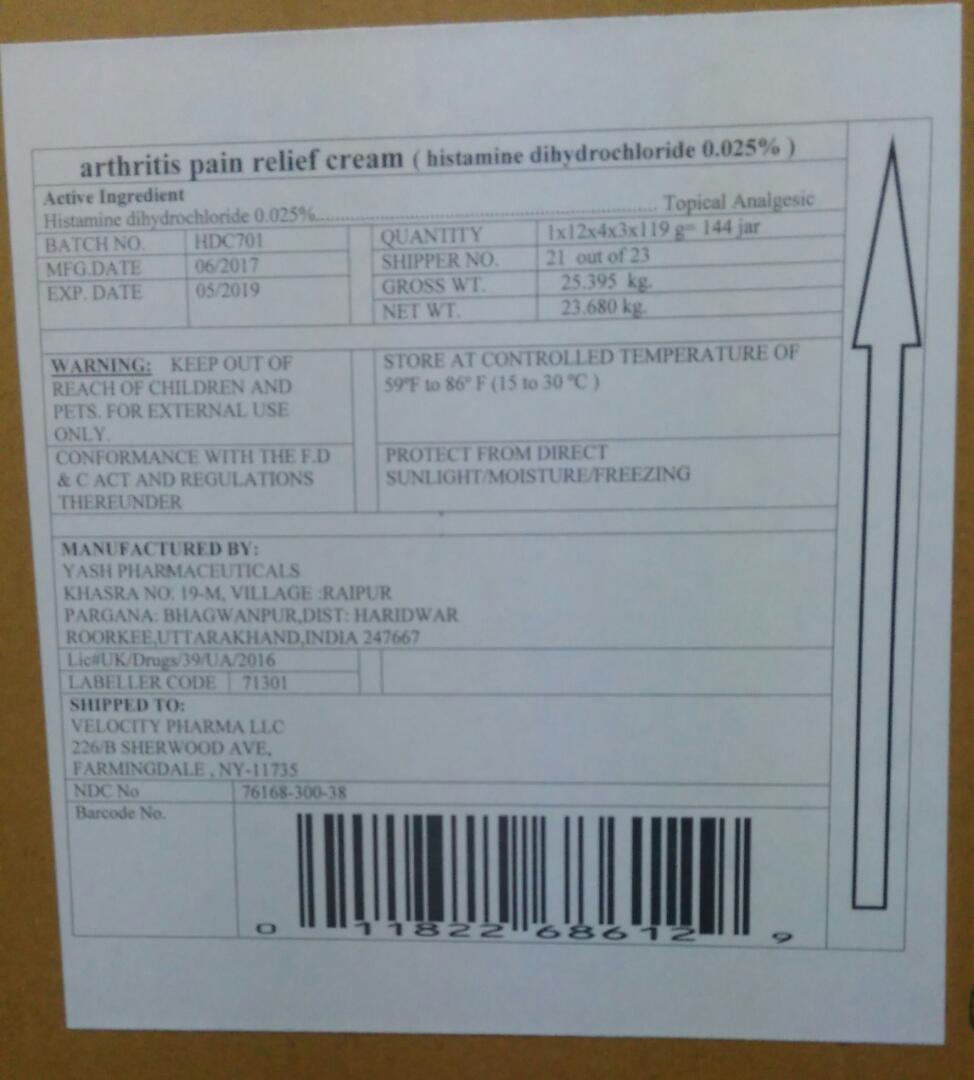 DRUG LABEL: Pain Relieving Arthritis
NDC: 71301-004 | Form: CREAM
Manufacturer: Yash Pharmceuticals
Category: otc | Type: HUMAN OTC DRUG LABEL
Date: 20170606

ACTIVE INGREDIENTS: HISTAMINE DIHYDROCHLORIDE 0.025 g/100 g
INACTIVE INGREDIENTS: ACRYLAMIDE; BUTYLATED HYDROXYTOLUENE; CETOSTEARYL ALCOHOL; DISODIUM HYDROGEN CITRATE; EDETATE SODIUM; GLUCOSAMINE SULFATE; GLYCERIN; ISOHEXADECANE; PROPYLENE GLYCOL; POLYSORBATE 80; SODIUM ACRYLATE/SODIUM ACRYLOYLDIMETHYLTAURATE COPOLYMER (4000000 MW); TITANIUM DIOXIDE; DIETHYLENE GLYCOL MONOETHYL ETHER; PETROLATUM; WATER

Pain Relieving Arthritis Cream- Bulk

Drug Facts

Active Ingredient

Histamine dihydrochloride ...... 0.025%

Purpose

External Analgesic

Uses

- For the temporary relief of minor aches and pains of muscles and joints associated with arthritis, simple backache, strains & bruises.

Warnings

- For external use only.
- Do not use on wounds or damaged skin or if you are allergic to ingredients in the product.

When using this product

- avoid contact with eyes. If product gets into eyes, rinse thoroughly with water.
- do not bandage tightly or use a heating pad.

Stop use and ask a doctor if

- rash appears.
- condition worsens, if symptoms persist for more than 7 days, or if symptoms clear up and occur again within a few days.

If pregnant or breast feeding,

ask a health professional before use.

Keep out of reach of children.

If swallowed, get medical help or contact a Poison Control Center right away.

Directions

- For Use by Adults and Children over 12 years.
- Apply a thin layer to pain site and massage until thoroughly absorbed into skin. Apply no more than 3 to 4 times daily.
- Children 12 years or younger consult a physician.

Other information

- Store between 40°F and 86°F (4°C and 30C).
- Tamper Evident Feature: do not use if outer shrink wrap on jar is torn, broken or missing.

Inactive ingredients

arylamide, butylated hydroxyl toluene, cetostearyl alcohol , cetomacrogol 1000, disodium EDTA, glucosamine sulfate, glycerin, isohexadecane, polysorbate 80, propylene glycol, sodium acrylodimethyl taurate copolymer, titanium dioxide, transquitol P, vitamin E acetate, white petroleum jelly, water

Questions or Comments? Call 1855-314-1850

Distributed by: Velocity Pharma LLC
Farmingdale, NY, 11735

PACKAGE LABEL

Pain Relieving Arthritis Cream

Net Wt. 4 oz (119g)-- Bulk of 144 in a case